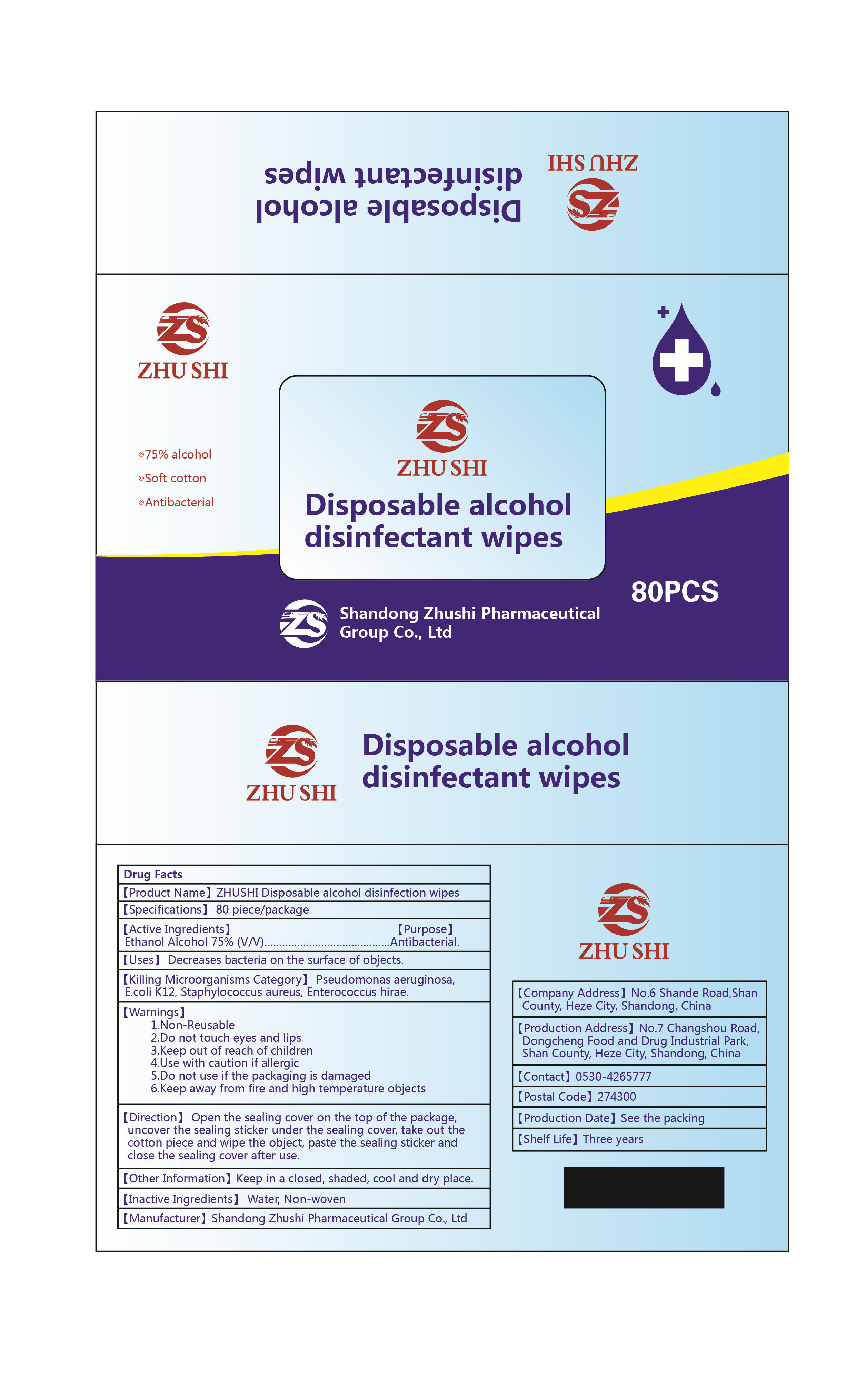 DRUG LABEL: ZHUSHI Disposable alcohol disinfectant wipes
NDC: 56040-012 | Form: CLOTH
Manufacturer: Shandong Zhushi Pharmaceutical Group Co., Ltd.
Category: otc | Type: HUMAN OTC DRUG LABEL
Date: 20220310

ACTIVE INGREDIENTS: ALCOHOL 75 mL/100 mL
INACTIVE INGREDIENTS: WATER

Direction

Open the sealing cover on the top of the package,uncover the sealing sticker under the sealing cover, take out thecotton piece and wipe the object, paste the sealing sticker andclose the sealing cover after use.

INACTIVE INGREDIENT

Water,non-woven

Uses

Decreases bacteria on the surface of objects.

ACTIVE INGREDIENT

ethanol alcohol 75%

keep out of reach of children

PURPOSE

Antibacterial

WARNINGS

1.Non-Reusable
2.Do not touch eyes and lips
3.Keep out of reach of children4.Use with caution if allergic
5.Do not use if the packaging is damaged
6.Keep away from fire and high temperature objects

STORAGE AND HANDLING

Keep in a closed, shaded, cool and dry place.